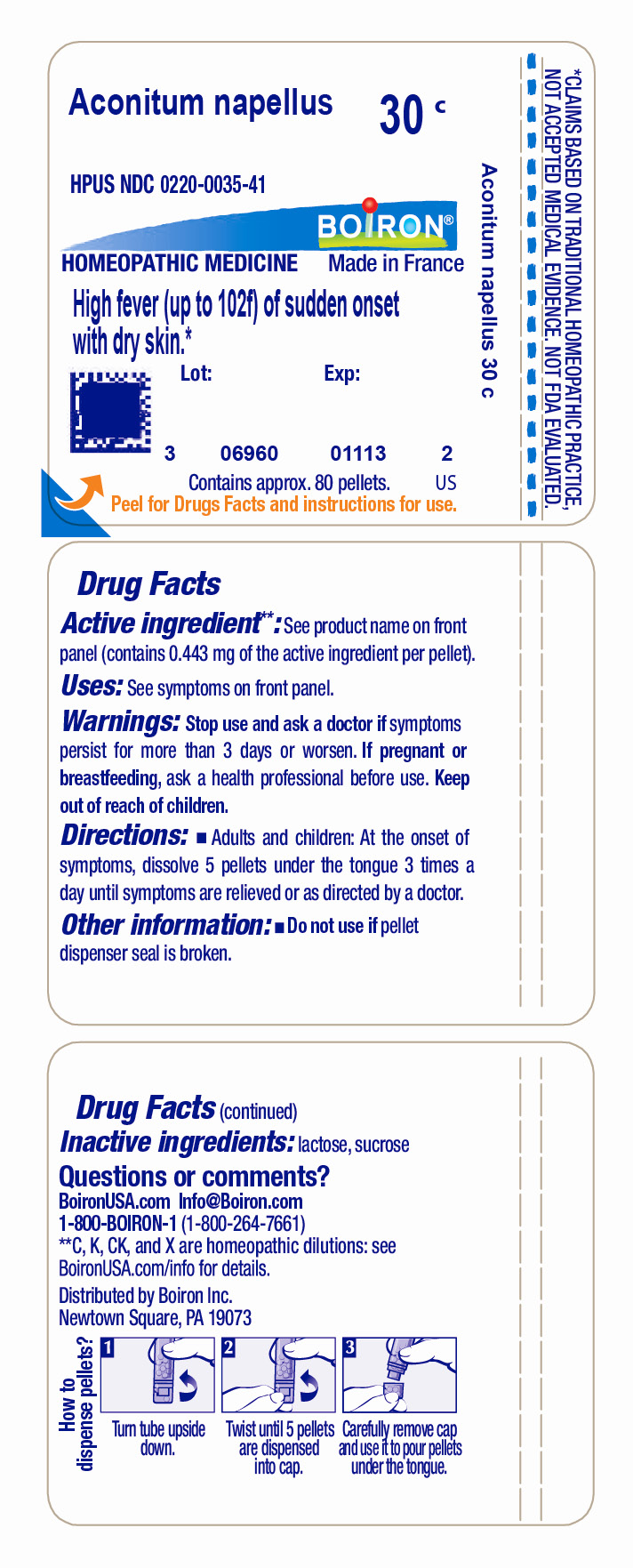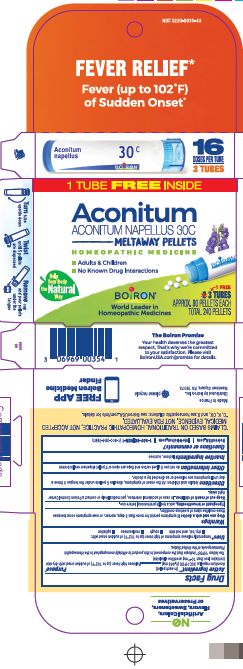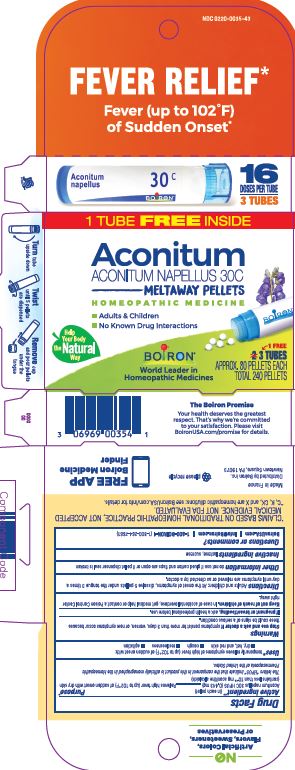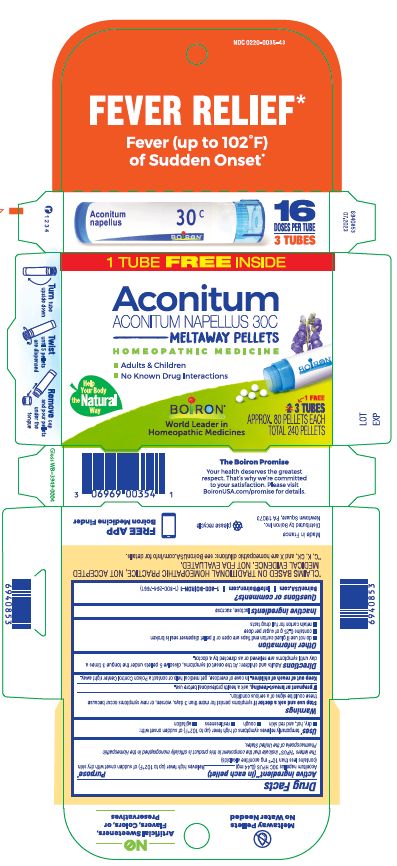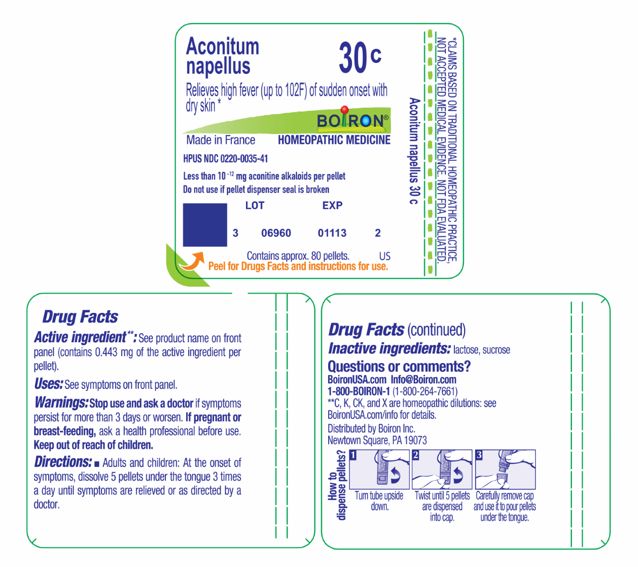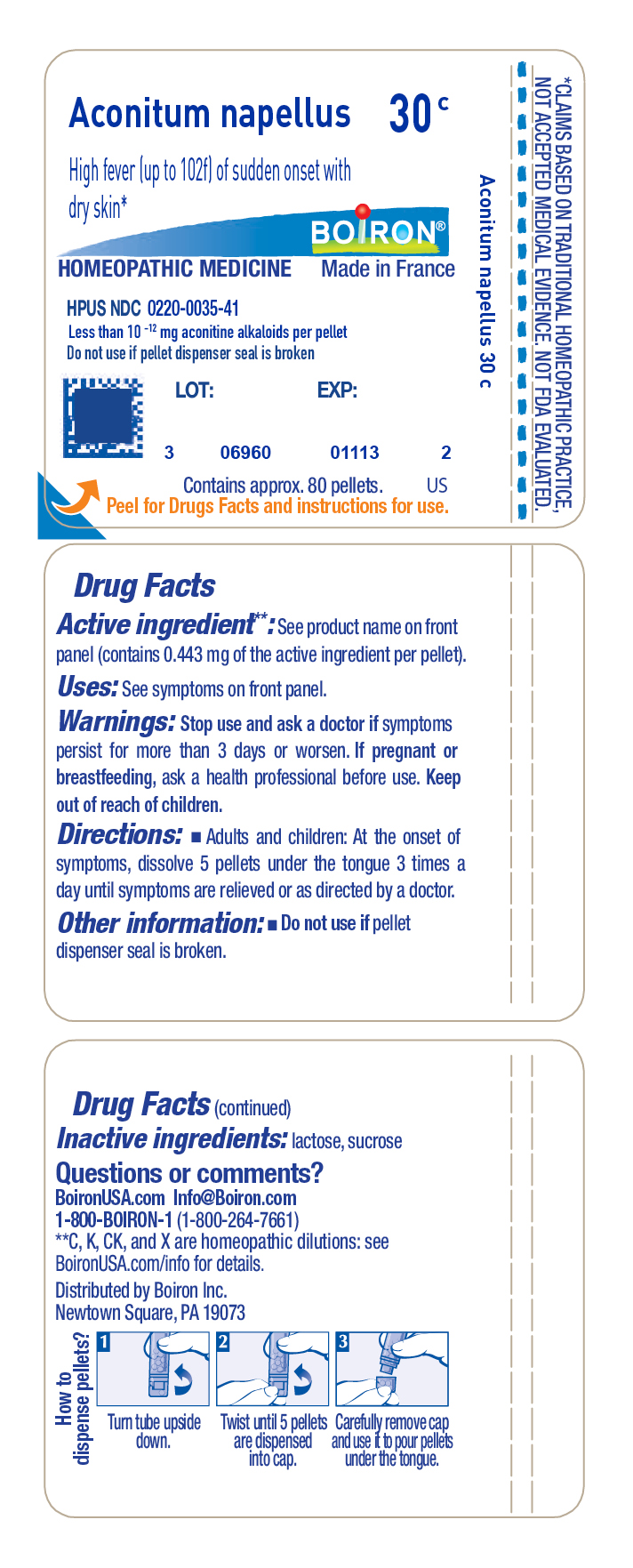 DRUG LABEL: Aconitum napellus
NDC: 0220-0035 | Form: PELLET
Manufacturer: Boiron
Category: homeopathic | Type: HUMAN OTC DRUG LABEL
Date: 20250910

ACTIVE INGREDIENTS: ACONITUM NAPELLUS 30 [hp_C]/30 [hp_C]
INACTIVE INGREDIENTS: SUCROSE; LACTOSE, UNSPECIFIED FORM

Aconitum napellus 30C

Active ingredient** (in each pellet)

Aconitum napellus 30C HPUS (**contains 0.443 mg of the active ingredient in each pellet)

(contains less than 10^-12 mg aconitine alkaloids)

The letters "HPUS" indicate that the component in this product are officially monographed in the Homeopathic Pharmacopoeia of the United States.

Purpose*

Relieves high fever (up to 102oF) of sudden onset with dry skin*

Uses*

Temporarily relieves symptoms of high fever (up to 102oF) of sudden onset with

- dry, hot, and red skin
- cough
- restlessness
- agitation

Stop use and ask a doctor if symptoms persist for more than 3 days, worsen, or new symptoms occur because these could be signs of a serious condition.

PREGNANCY OR BREAST FEEDING

If pregnant or breast-feeding, ask a health professional before use.

Keep out of reach of children. In case of accidental overdose, get medical help or contact a Poison Control Center right away.

DOSAGE AND ADMINISTRATION

Adults and children: At the onset of symptoms, dissolve 5 pellets under the tongue 3 times a day until symptoms are relieved or as directed by a doctor.

INACTIVE INGREDIENT

lactose, sucrose

QUESTIONS

BoironUSA.com Info@boiron.com

1-800-BOIRON-1 (1-800-264-7661),

Distributed by Boiron, Inc.

Newtown Square, PA 19073

Made in France

Do not use if pellet dispenser seal is broken.

Do not use if glued carton end flaps are open or if pellet dispenser seal is broken.

contains 0.25 g of sugar per dose

retain carton for full drug facts

Approx. 80 Pellets each

Total 240 Pellets

How to dispense pellets? Turn tube upside down. Twist until 5 pellets are dispensed. Remove cap and pour pellets under the tongue.

Fever Relief*

No Known Drug Interactions

*CLAIMS BASED ON TRADITIONAL HOMEOPATHIC PRACTICE NOT ACCEPTED MEDICAL EVIDENCE. NOT FDA EVALUATED.

*C,K,CK, and X are homeopathic dilutions: see BoironUSA.com/info for details.